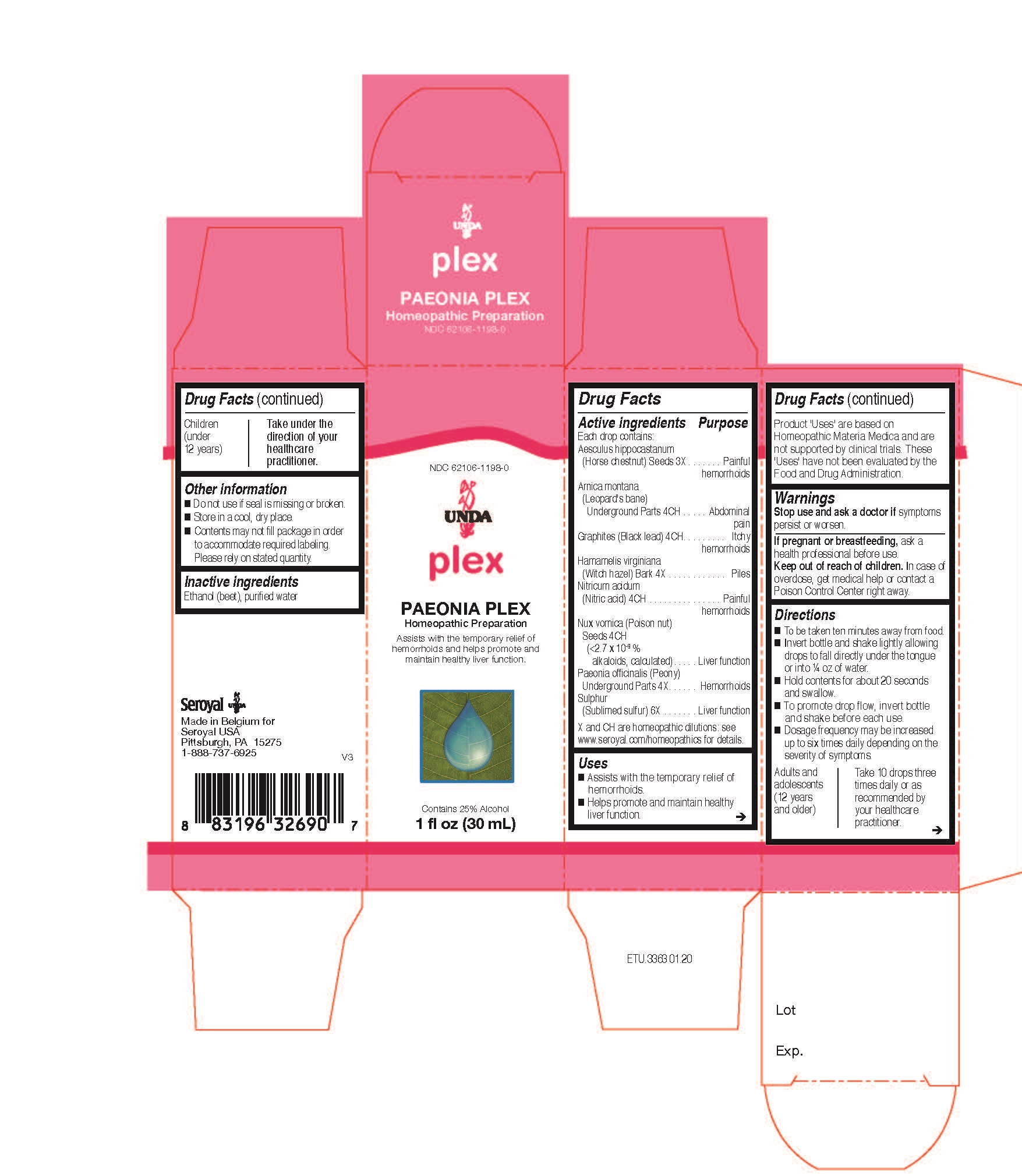 DRUG LABEL: PAEONIA Plex
NDC: 62106-1198 | Form: LIQUID
Manufacturer: Seroyal USA
Category: homeopathic | Type: HUMAN OTC DRUG LABEL
Date: 20201009

ACTIVE INGREDIENTS: ARNICA MONTANA ROOT 4 [hp_C]/30 mL; GRAPHITE 4 [hp_C]/30 mL; HAMAMELIS VIRGINIANA BARK 4 [hp_X]/30 mL; PAEONIA OFFICINALIS ROOT 4 [hp_X]/30 mL; SULFUR 6 [hp_X]/30 mL; STRYCHNOS NUX-VOMICA SEED 4 [hp_C]/30 mL; NITRIC ACID 4 [hp_C]/30 mL; HORSE CHESTNUT 3 [hp_X]/30 mL
INACTIVE INGREDIENTS: ALCOHOL; WATER

PAEONIA Plex

Active ingredients

Each drop contains:
Aesculus hippocastanum (Horse chestnut) Seeds 3X
Arnica montana (Leopard's bane) Underground Parts 4CH
Graphites (Black lead) 4CH
Hamamelis virginiana (Witch hazel) Bark 4X
Nitricum acidum (Nitric acid) 4CH
Nux vomica (Poison nut) Seeds 4CH (<2.7 x 10-9 % alkaloids, calculated)
Paeonia officinalis (Peony) Underground Parts 4X
Sulphur (Sublimed sulfur) 6X

Uses

Assists with the temporary relief of hemorrhoids.
Helps promote and maintain healthy liver function.

Warnings
Stop use and ask a doctor if symptoms persist or worsen.

If pregnant or breastfeeding, ask a health professional before use.
Keep out of reach of children.

In case of overdose, get medical help or contact a Poison Control Center right away.

Stop use and ask a doctor if symptoms persist or worsen.

PREGNANCY OR BREAST FEEDING

If pregnant or breastfeeding, ask a health professional before use.

Keep out of reach of children.

OVERDOSAGE

In case of overdose, get medical help or contact a Poison Control Center right away.

Other information
Do not use if seal is missing or broken.
Store in a cool, dry place.

Contents may not fill package in order to accommodate required labeling. Please rely on stated quantity

Inactive ingredients

Ethanol (beet), purified water

Directions
To be taken ten minutes away from food.
Invert bottle and shake lightly allowing drops to fall directly under the tongue or into ¼ oz of water.
Hold contents for about 20 seconds and swallow.
To promote drop flow, invert bottle and shake before each use.
Dosage frequency may be increased up to six times daily depending on the severity of symptoms.

Adults and adolescents (12 years and older)

Take 10 drops three times daily or as recommended by your healthcare practitioner

Children (under 12 years)

Take under the direction of your healthcare practitioner.

Uses

Assists with the temporary relief of hemorrhoids.
Helps promote and maintain healthy liver function.

Directions

To be taken ten minutes away from food.
Invert bottle and shake lightly allowing drops to fall directly under the tongue or into ¼ oz of water.
Hold contents for about 20 seconds and swallow.
To promote drop flow, invert bottle and shake before each use.
Dosage frequency may be increased up to six times daily depending on the severity of symptoms.

Adults and adolescents (12 years and older)

Take 10 drops three times daily or as recommended by your healthcare practitioner.

Children (under 12 years)

Take under the direction of your healthcare practitioner.

PACKAGE LABEL

NDC 62106-1198-0

UNDA

Plex

PAEONIA PLEX

Homeopathic Preparation

Assists with the temporary relief of
hemorrhoids and helps promote and
maintain healthy liver function.

Contains 25% Alcohol

1 fl oz (30 mL)